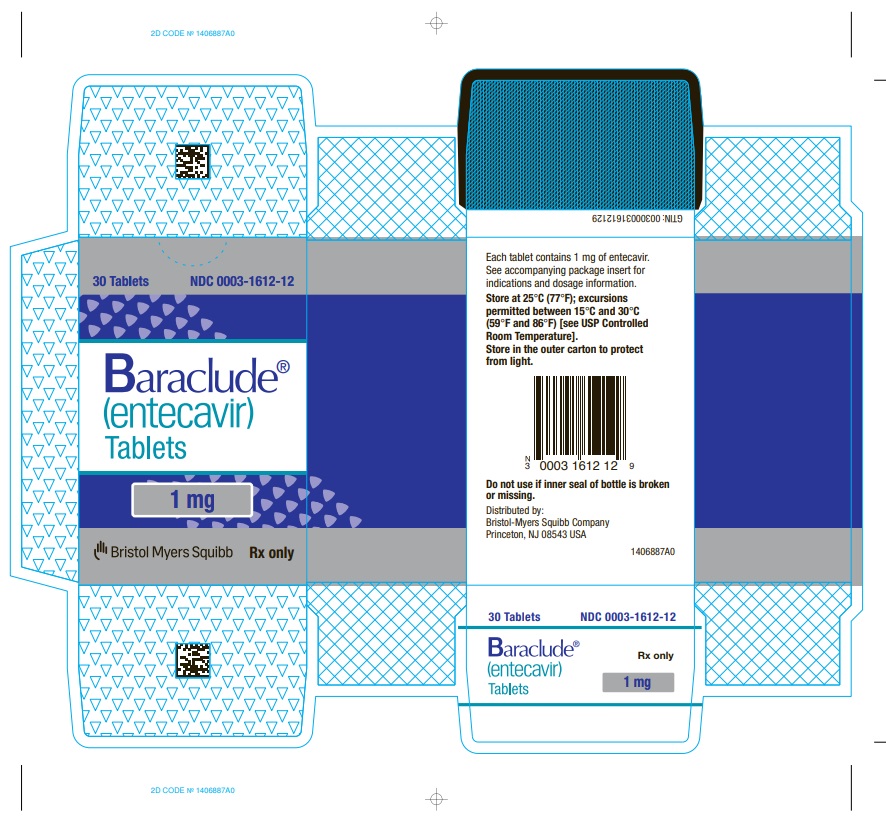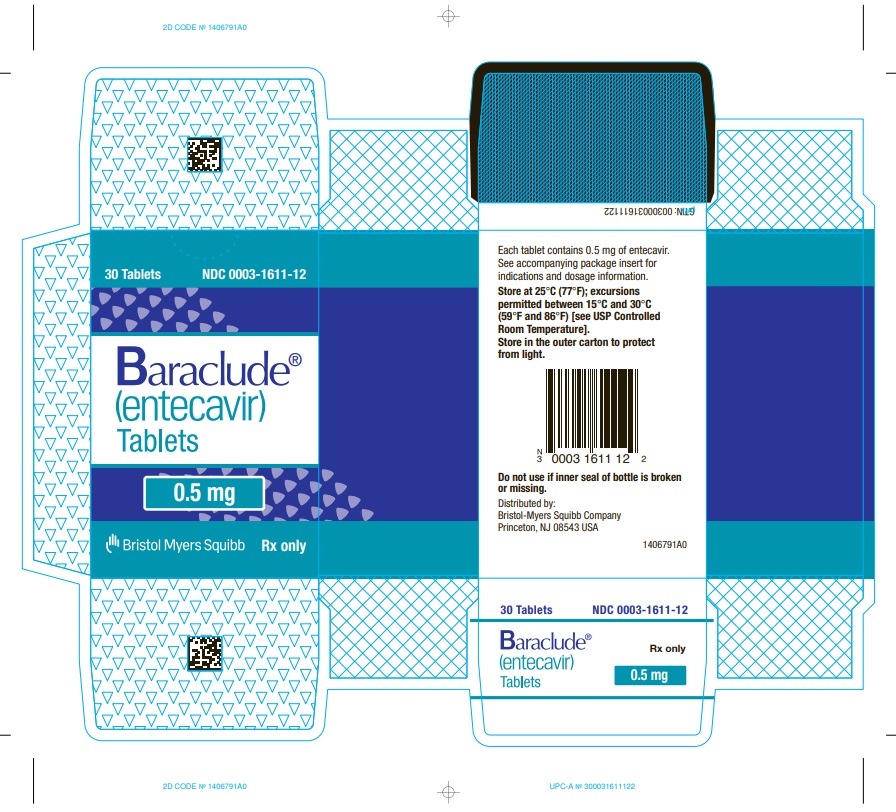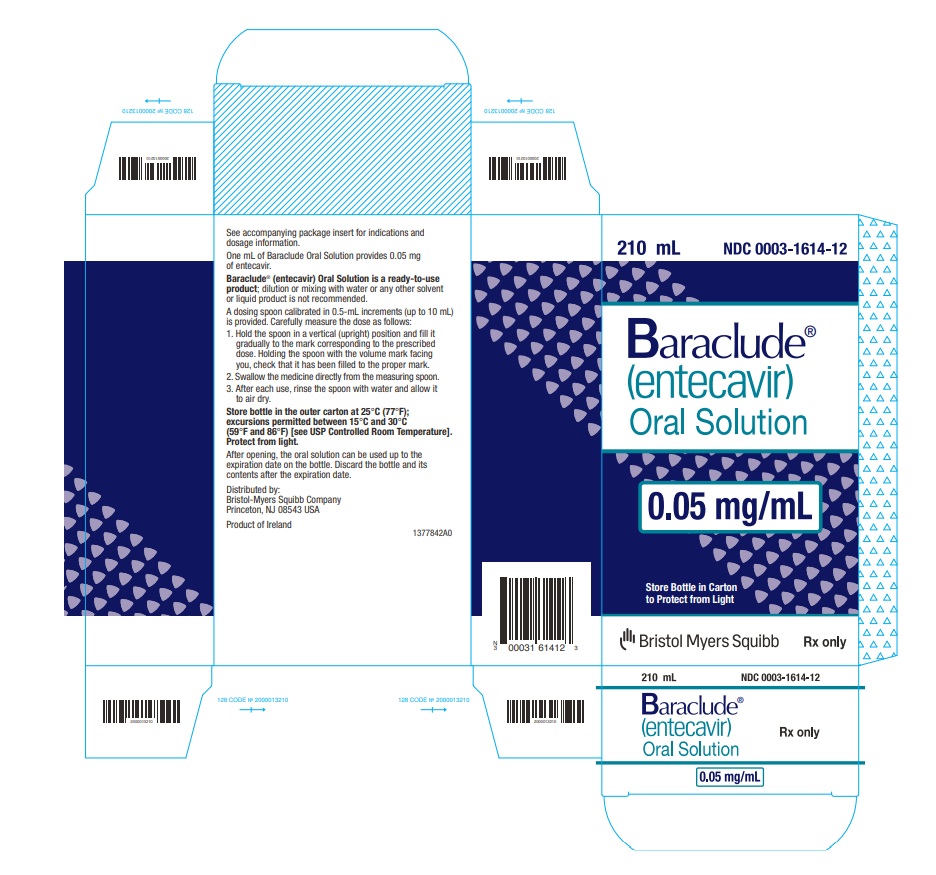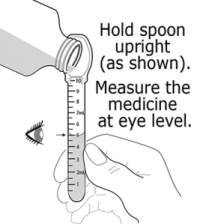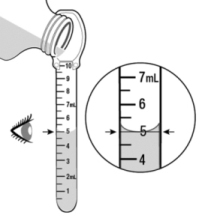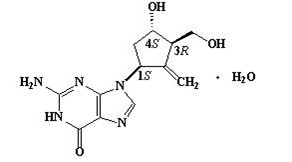 DRUG LABEL: BARACLUDE
NDC: 0003-1611 | Form: TABLET, FILM COATED
Manufacturer: E.R. Squibb & Sons, L.L.C.
Category: prescription | Type: HUMAN PRESCRIPTION DRUG LABEL
Date: 20191106

ACTIVE INGREDIENTS: entecavir 0.5 mg/1 1
INACTIVE INGREDIENTS: lactose monohydrate; MICROCRYSTALLINE CELLULOSE; POVIDONE, UNSPECIFIED; magnesium stearate; titanium dioxide; HYPROMELLOSE, UNSPECIFIED; polyethylene glycol 400; polysorbate 80; CROSPOVIDONE (120 .MU.M)

HIGHLIGHTS OF PRESCRIBING INFORMATION

These highlights do not include all the information needed to use BARACLUDE safely and effectively. See full prescribing information for BARACLUDE.
BARACLUDE® (entecavir) tablets, for oral use
BARACLUDE® (entecavir) oral solution
Initial U.S. Approval: 2005

WARNING: SEVERE ACUTE EXACERBATIONS OF HEPATITIS B, PATIENTS CO-INFECTED WITH HIV AND HBV, and LACTIC ACIDOSIS AND HEPATOMEGALY

See full prescribing information for complete boxed warning.

- Severe acute exacerbations of hepatitis B have been reported in patients who have discontinued anti-hepatitis B therapy, including entecavir. Hepatic function should be monitored closely for at least several months after discontinuation. Initiation of anti-hepatitis B therapy may be warranted. (5.1)
- BARACLUDE is not recommended for patients co-infected with human immunodeficiency virus (HIV) and hepatitis B virus (HBV) who are not also receiving highly active antiretroviral therapy (HAART), because of the potential for the development of resistance to HIV nucleoside reverse transcriptase inhibitors. (5.2)
- Lactic acidosis and severe hepatomegaly with steatosis, including fatal cases, have been reported with the use of nucleoside analogue inhibitors. (5.3)

1 INDICATIONS AND USAGE

BARACLUDE is a hepatitis B virus nucleoside analogue reverse transcriptase inhibitor indicated for the treatment of chronic hepatitis B virus infection in adults and children at least 2 years of age with evidence of active viral replication and either evidence of persistent elevations in serum aminotransferases (ALT or AST) or histologically active disease. (1)

2 DOSAGE AND ADMINISTRATION

- Nucleoside-inhibitor-treatment-naïve with compensated liver disease (greater than or equal to 16 years old): 0.5 mg once daily. (2.2)
- Nucleoside-inhibitor-treatment-naïve and lamivudine-experienced pediatric patients at least 2 years of age and weighing at least 10 kg: dosing is based on weight. (2.3)
- Lamivudine-refractory or known lamivudine or telbivudine resistance substitutions (greater than or equal to 16 years old): 1 mg once daily. (2.2)
- Decompensated liver disease (adults): 1 mg once daily. (2.2)
- Renal impairment: Dosage adjustment is recommended if creatinine clearance is less than 50 mL/min. (2.4)
- BARACLUDE should be administered on an empty stomach. (2.1)

3 DOSAGE FORMS AND STRENGTHS

- Tablets: 0.5 mg and 1 mg (3, 16)
- Oral solution: 0.05 mg/mL (3, 16)

4 CONTRAINDICATIONS

- None. (4)

5 WARNINGS AND PRECAUTIONS

- Severe acute exacerbations of hepatitis B virus infection after discontinuation: Monitor hepatic function closely for at least several months. (5.1, 6.1)
- Co-infection with HIV: BARACLUDE is not recommended unless the patient is also receiving HAART. (5.2)
- Lactic acidosis and severe hepatomegaly with steatosis: If suspected, treatment should be suspended. (5.3)

6 ADVERSE REACTIONS

- In adults, the most common adverse reactions (≥3%, all severity grades) are headache, fatigue, dizziness, and nausea. The adverse reactions observed in pediatric patients were consistent with those observed in adults. (6.1)

To report SUSPECTED ADVERSE REACTIONS, contact Bristol-Myers Squibb at 1-800-721-5072 or FDA at 1-800-FDA-1088 or www.fda.gov/medwatch.

8 USE IN SPECIFIC POPULATIONS

- Liver transplant recipients: Limited data on safety and efficacy are available. (8.8)

FULL PRESCRIBING INFORMATION

WARNING: SEVERE ACUTE EXACERBATIONS OF HEPATITIS B, PATIENTS CO-INFECTED WITH HIV AND HBV, and LACTIC ACIDOSIS AND HEPATOMEGALY

Severe acute exacerbations of hepatitis B have been reported in patients who have discontinued anti-hepatitis B therapy, including entecavir. Hepatic function should be monitored closely with both clinical and laboratory follow-up for at least several months in patients who discontinue anti-hepatitis B therapy. If appropriate, initiation of anti-hepatitis B therapy may be warranted [see Warnings and Precautions (5.1)].

Limited clinical experience suggests there is a potential for the development of resistance to HIV (human immunodeficiency virus) nucleoside reverse transcriptase inhibitors if BARACLUDE is used to treat chronic hepatitis B virus (HBV) infection in patients with HIV infection that is not being treated. Therapy with BARACLUDE is not recommended for HIV/HBV co-infected patients who are not also receiving highly active antiretroviral therapy (HAART) [see Warnings and Precautions (5.2)].

Lactic acidosis and severe hepatomegaly with steatosis, including fatal cases, have been reported with the use of nucleoside analogue inhibitors alone or in combination with antiretrovirals [see Warnings and Precautions (5.3)].

1 INDICATIONS AND USAGE

BARACLUDE® (entecavir) is indicated for the treatment of chronic hepatitis B virus infection in adults and pediatric patients 2 years of age and older with evidence of active viral replication and either evidence of persistent elevations in serum aminotransferases (ALT or AST) or histologically active disease.

2 DOSAGE AND ADMINISTRATION

2.1 Timing of Administration

BARACLUDE should be administered on an empty stomach (at least 2 hours after a meal and 2 hours before the next meal).

2.2 Recommended Dosage in Adults

Compensated Liver Disease

The recommended dose of BARACLUDE for chronic hepatitis B virus infection in nucleoside-inhibitor-treatment-naïve adults and adolescents 16 years of age and older is 0.5 mg once daily.

The recommended dose of BARACLUDE in adults and adolescents (at least 16 years of age) with a history of hepatitis B viremia while receiving lamivudine or known lamivudine or telbivudine resistance substitutions rtM204I/V with or without rtL180M, rtL80I/V, or rtV173L is 1 mg once daily.

Decompensated Liver Disease

The recommended dose of BARACLUDE for chronic hepatitis B virus infection in adults with decompensated liver disease is 1 mg once daily.

2.3 Recommended Dosage in Pediatric Patients

Table 1 describes the recommended dose of BARACLUDE for pediatric patients 2 years of age or older and weighing at least 10 kg. The oral solution should be used for patients with body weight up to 30 kg.

Table 1: Dosing Schedule for Pediatric Patients
 | Recommended Once-Daily Dose of Oral Solution (mL)
Body Weight (kg) | Treatment-Naïve; Patientsa | Lamivudine-Experienced; Patientsb
10 to 11 | 3 | 6
greater than 11 to 14 | 4 | 8
greater than 14 to 17 | 5 | 10
greater than 17 to 20 | 6 | 12
greater than 20 to 23 | 7 | 14
greater than 23 to 26 | 8 | 16
greater than 26 to 30 | 9 | 18
greater than 30 | 10 | 20
a Children with body weight greater than 30 kg should receive 10 mL (0.5 mg) of oral solution or one 0.5 mg tablet once daily.
b Children with body weight greater than 30 kg should receive 20 mL (1 mg) of oral solution or one 1 mg tablet once daily.

2.4 Renal Impairment

In adult subjects with renal impairment, the apparent oral clearance of entecavir decreased as creatinine clearance decreased [see Clinical Pharmacology (12.3)]. Dosage adjustment is recommended for patients with creatinine clearance less than 50 mL/min, including patients on hemodialysis or continuous ambulatory peritoneal dialysis (CAPD), as shown in Table 2. The once-daily dosing regimens are preferred.

Table 2: Recommended Dosage of BARACLUDE in Adult Patients with Renal Impairment
Creatinine Clearance (mL/min) | Usual Dose (0.5 mg) | Lamivudine-Refractory or Decompensated Liver Disease (1 mg)
50 or greater | 0.5 mg once daily | 1 mg once daily
30 to less than 50 | 0.25 mg once dailya; OR; 0.5 mg every 48 hours | 0.5 mg once daily; OR; 1 mg every 48 hours
10 to less than 30 | 0.15 mg once dailya; OR; 0.5 mg every 72 hours | 0.3 mg once dailya; OR; 1 mg every 72 hours
Less than 10; Hemodialysisb or CAPD | 0.05 mg once dailya; OR; 0.5 mg every 7 days | 0.1 mg once dailya; OR; 1 mg every 7 days
a For doses less than 0.5 mg, BARACLUDE Oral Solution is recommended.
b If administered on a hemodialysis day, administer BARACLUDE after the hemodialysis session.

Although there are insufficient data to recommend a specific dose adjustment of BARACLUDE in pediatric patients with renal impairment, a reduction in the dose or an increase in the dosing interval similar to adjustments for adults should be considered.

2.5 Hepatic Impairment

No dosage adjustment is necessary for patients with hepatic impairment.

2.6 Duration of Therapy

The optimal duration of treatment with BARACLUDE for patients with chronic hepatitis B virus infection and the relationship between treatment and long-term outcomes such as cirrhosis and hepatocellular carcinoma are unknown.

3 DOSAGE FORMS AND STRENGTHS

- BARACLUDE 0.5 mg film-coated tablets are white to off-white, triangular-shaped, and debossed with “BMS” on one side and “1611” on the other side.
- BARACLUDE 1 mg film-coated tablets are pink, triangular-shaped, and debossed with “BMS” on one side and “1612” on the other side.
- BARACLUDE oral solution, 0.05 mg/mL, is a ready-to-use, orange-flavored, clear, colorless to pale yellow, aqueous solution. Ten milliliters of the oral solution provides a 0.5 mg dose and 20 mL provides a 1 mg dose of entecavir.

4 CONTRAINDICATIONS

None.

5 WARNINGS AND PRECAUTIONS

5.1 Severe Acute Exacerbations of Hepatitis B

Severe acute exacerbations of hepatitis B have been reported in patients who have discontinued anti-hepatitis B therapy, including entecavir [see Adverse Reactions (6.1)]. Hepatic function should be monitored closely with both clinical and laboratory follow-up for at least several months in patients who discontinue anti-hepatitis B therapy. If appropriate, initiation of anti-hepatitis B therapy may be warranted.

5.2 Patients Co-infected with HIV and HBV

BARACLUDE has not been evaluated in HIV/HBV co-infected patients who were not simultaneously receiving effective HIV treatment. Limited clinical experience suggests there is a potential for the development of resistance to HIV nucleoside reverse transcriptase inhibitors if BARACLUDE is used to treat chronic hepatitis B virus infection in patients with HIV infection that is not being treated [see Microbiology (12.4)]. Therefore, therapy with BARACLUDE is not recommended for HIV/HBV co-infected patients who are not also receiving HAART. Before initiating BARACLUDE therapy, HIV antibody testing should be offered to all patients. BARACLUDE has not been studied as a treatment for HIV infection and is not recommended for this use.

5.3 Lactic Acidosis and Severe Hepatomegaly with Steatosis

Lactic acidosis and severe hepatomegaly with steatosis, including fatal cases, have been reported with the use of nucleoside analogue inhibitors, including BARACLUDE, alone or in combination with antiretrovirals. A majority of these cases have been in women. Obesity and prolonged nucleoside inhibitor exposure may be risk factors. Particular caution should be exercised when administering nucleoside analogue inhibitors to any patient with known risk factors for liver disease; however, cases have also been reported in patients with no known risk factors.

Lactic acidosis with BARACLUDE use has been reported, often in association with hepatic decompensation, other serious medical conditions, or drug exposures. Patients with decompensated liver disease may be at higher risk for lactic acidosis. Treatment with BARACLUDE should be suspended in any patient who develops clinical or laboratory findings suggestive of lactic acidosis or pronounced hepatotoxicity (which may include hepatomegaly and steatosis even in the absence of marked transaminase elevations).

6 ADVERSE REACTIONS

The following adverse reactions are discussed in other sections of the labeling:

- Exacerbations of hepatitis after discontinuation of treatment [see Boxed Warning, Warnings and Precautions (5.1)].
- Lactic acidosis and severe hepatomegaly with steatosis [see Boxed Warning, Warnings and Precautions (5.3)].

6.1 Clinical Trial Experience

Because clinical trials are conducted under widely varying conditions, adverse reaction rates observed in the clinical trials of a drug cannot be directly compared to rates in the clinical trials of another drug and may not reflect the rates observed in practice.

Clinical Trial Experience in Adults

Compensated Liver Disease

Assessment of adverse reactions is based on four studies (AI463014, AI463022, AI463026, and AI463027) in which 1720 subjects with chronic hepatitis B virus infection and compensated liver disease received double-blind treatment with BARACLUDE 0.5 mg/day (n=679), BARACLUDE 1 mg/day (n=183), or lamivudine (n=858) for up to 2 years. Median duration of therapy was 69 weeks for BARACLUDE-treated subjects and 63 weeks for lamivudine-treated subjects in Studies AI463022 and AI463027 and 73 weeks for BARACLUDE-treated subjects and 51 weeks for lamivudine-treated subjects in Studies AI463026 and AI463014. The safety profiles of BARACLUDE and lamivudine were comparable in these studies.

The most common adverse reactions of any severity (≥3%) with at least a possible relation to study drug for BARACLUDE-treated subjects were headache, fatigue, dizziness, and nausea. The most common adverse reactions among lamivudine-treated subjects were headache, fatigue, and dizziness. One percent of BARACLUDE-treated subjects in these four studies compared with 4% of lamivudine-treated subjects discontinued for adverse events or abnormal laboratory test results.

Clinical adverse reactions of moderate-severe intensity and considered at least possibly related to treatment occurring during therapy in four clinical studies in which BARACLUDE was compared with lamivudine are presented in Table 3.

Table 3: Clinical Adverse Reactionsa of Moderate-Severe Intensity (Grades 2‑4) Reported in Four Entecavir Clinical Trials Through 2 Years
 | Nucleoside-Inhibitor‑Naïveb |  | Lamivudine- Refractoryc
Body System/; Adverse Reaction | BARACLUDE; 0.5 mg; n=679 | Lamivudine; 100 mg; n=668 | BARACLUDE; 1 mg; n=183 | Lamivudine; 100 mg; n=190
Any Grade 2–4 adverse reactiona | 15% | 18% | 22% | 23%
Gastrointestinal
Diarrhea | <1% | 0 | 1% | 0
Dyspepsia | <1% | <1% | 1% | 0
Nausea | <1% | <1% | <1% | 2%
Vomiting | <1% | <1% | <1% | 0
General
Fatigue | 1% | 1% | 3% | 3%
Nervous System
Headache | 2% | 2% | 4% | 1%
Dizziness | <1% | <1% | 0 | 1%
Somnolence | <1% | <1% | 0 | 0
Psychiatric
Insomnia | <1% | <1% | 0 | <1%
a Includes events of possible, probable, certain, or unknown relationship to treatment regimen.
b Studies AI463022 and AI463027.
c Includes Study AI463026 and the BARACLUDE 1 mg and lamivudine treatment arms of Study AI463014, a Phase 2 multinational, randomized, double-blind study of three doses of BARACLUDE (0.1, 0.5, and 1 mg) once daily versus continued lamivudine 100 mg once daily for up to 52 weeks in subjects who experienced recurrent viremia on lamivudine therapy.

Laboratory Abnormalities

Frequencies of selected treatment-emergent laboratory abnormalities reported during therapy in four clinical trials of BARACLUDE compared with lamivudine are listed in Table 4.

Table 4: Selected Treatment-Emergenta Laboratory Abnormalities Reported in Four Entecavir Clinical Trials Through 2 Years
 | Nucleoside-Inhibitor-Naïveb |  | Lamivudine-Refractoryc
Test | BARACLUDE; 0.5 mg; n=679 | Lamivudine; 100 mg; n=668 | BARACLUDE; 1 mg; n=183 | Lamivudine; 100 mg; n=190
Any Grade 3–4 laboratory abnormalityd | 35% | 36% | 37% | 45%
ALT >10 × ULN and >2 × baseline | 2% | 4% | 2% | 11%
ALT >5 × ULN | 11% | 16% | 12% | 24%
Albumin <2.5 g/dL | <1% | <1% | 0 | 2%
Total bilirubin >2.5 × ULN | 2% | 2% | 3% | 2%
Lipase ≥2.1 × ULN | 7% | 6% | 7% | 7%
Creatinine >3 × ULN | 0 | 0 | 0 | 0
Confirmed creatinine increase ≥0.5 mg/dL | 1% | 1% | 2% | 1%
Hyperglycemia, fasting >250 mg/dL | 2% | 1% | 3% | 1%
Glycosuriae | 4% | 3% | 4% | 6%
Hematuriaf | 9% | 10% | 9% | 6%
Platelets <50,000/mm^3 | <1% | <1% | <1% | <1%
a On-treatment value worsened from baseline to Grade 3 or Grade 4 for all parameters except albumin (any on-treatment value <2.5 g/dL), confirmed creatinine increase ≥0.5 mg/dL, and ALT >10 × ULN and >2 × baseline.
b Studies AI463022 and AI463027.
c Includes Study AI463026 and the BARACLUDE 1 mg and lamivudine treatment arms of Study AI463014, a Phase 2 multinational, randomized, double-blind study of three doses of BARACLUDE (0.1, 0.5, and 1 mg) once daily versus continued lamivudine 100 mg once daily for up to 52 weeks in subjects who experienced recurrent viremia on lamivudine therapy.
d Includes hematology, routine chemistries, renal and liver function tests, pancreatic enzymes, and urinalysis.
e Grade 3 = 3+, large, ≥500 mg/dL; Grade 4 = 4+, marked, severe.
f Grade 3 = 3+, large; Grade 4 = ≥4+, marked, severe, many.
ULN=upper limit of normal.

Among BARACLUDE-treated subjects in these studies, on-treatment ALT elevations greater than 10 times the upper limit of normal (ULN) and greater than 2 times baseline generally resolved with continued treatment. A majority of these exacerbations were associated with a ≥2 log10/mL reduction in viral load that preceded or coincided with the ALT elevation. Periodic monitoring of hepatic function is recommended during treatment.

Exacerbations of Hepatitis After Discontinuation of Treatment

An exacerbation of hepatitis or ALT flare was defined as ALT greater than 10 times ULN and greater than 2 times the subject’s reference level (minimum of the baseline or last measurement at end of dosing). For all subjects who discontinued treatment (regardless of reason), Table 5 presents the proportion of subjects in each study who experienced post-treatment ALT flares. In these studies, a subset of subjects was allowed to discontinue treatment at or after 52 weeks if they achieved a protocol-defined response to therapy. If BARACLUDE is discontinued without regard to treatment response, the rate of post-treatment flares could be higher. [See Warnings and Precautions (5.1).]

Table 5: Exacerbations of Hepatitis During Off-Treatment Follow-up, Subjects in Studies AI463022, AI463027, and AI463026
 | Subjects with ALT Elevations >10 × ULN and >2 × Referencea
 | BARACLUDE | Lamivudine
Nucleoside-inhibitor-naïve
HBeAg-positive | 4/174 (2%) | 13/147 (9%)
HBeAg-negative | 24/302 (8%) | 30/270 (11%)
Lamivudine-refractory | 6/52 (12%) | 0/16
a Reference is the minimum of the baseline or last measurement at end of dosing. Median time to off-treatment exacerbation was 23 weeks for BARACLUDE-treated subjects and 10 weeks for lamivudine-treated subjects.

Decompensated Liver Disease

Study AI463048 was a randomized, open-label study of BARACLUDE 1 mg once daily versus adefovir dipivoxil 10 mg once daily given for up to 48 weeks in adult subjects with chronic HBV infection and evidence of hepatic decompensation, defined as a Child-Turcotte-Pugh (CTP) score of 7 or higher [see Clinical Studies (14.1)]. Among the 102 subjects receiving BARACLUDE, the most common treatment-emergent adverse events of any severity, regardless of causality, occurring through Week 48 were peripheral edema (16%), ascites (15%), pyrexia (14%), hepatic encephalopathy (10%), and upper respiratory infection (10%). Clinical adverse reactions not listed in Table 3 that were observed through Week 48 include blood bicarbonate decreased (2%) and renal failure (<1%).

Eighteen of 102 (18%) subjects treated with BARACLUDE and 18/89 (20%) subjects treated with adefovir dipivoxil died during the first 48 weeks of therapy. The majority of deaths (11 in the BARACLUDE group and 16 in the adefovir dipivoxil group) were due to liver-related causes such as hepatic failure, hepatic encephalopathy, hepatorenal syndrome, and upper gastrointestinal hemorrhage. The rate of hepatocellular carcinoma (HCC) through Week 48 was 6% (6/102) for subjects treated with BARACLUDE and 8% (7/89) for subjects treated with adefovir dipivoxil. Five percent of subjects in either treatment arm discontinued therapy due to an adverse event through Week 48.

No subject in either treatment arm experienced an on-treatment hepatic flare (ALT >2 × baseline and >10 × ULN) through Week 48. Eleven of 102 (11%) subjects treated with BARACLUDE and 11/89 (13%) subjects treated with adefovir dipivoxil had a confirmed increase in serum creatinine of 0.5 mg/dL through Week 48.

HIV/HBV Co-infected

The safety profile of BARACLUDE 1 mg (n=51) in HIV/HBV co-infected subjects enrolled in Study AI463038 was similar to that of placebo (n=17) through 24 weeks of blinded treatment and similar to that seen in non-HIV infected subjects [see Warnings and Precautions (5.2)].

Liver Transplant Recipients

Among 65 subjects receiving BARACLUDE in an open-label, post-liver transplant trial [see Use in Specific Populations (8.8)], the frequency and nature of adverse events were consistent with those expected in patients who have received a liver transplant and the known safety profile of BARACLUDE.

Clinical Trial Experience in Pediatric Subjects

The safety of BARACLUDE in pediatric subjects 2 to less than 18 years of age is based on two clinical trials in subjects with chronic HBV infection (one Phase 2 pharmacokinetic trial [AI463028] and one Phase 3 trial [AI463189]). These trials provided experience in 168 HBeAg-positive subjects treated with BARACLUDE for a median duration of 72 weeks. The adverse reactions observed in pediatric subjects who received treatment with BARACLUDE were consistent with those observed in clinical trials of BARACLUDE in adults. Adverse drug reactions reported in greater than 1% of pediatric subjects included abdominal pain, rash events, poor palatability (“product taste abnormal”), nausea, diarrhea, and vomiting.

6.2 Postmarketing Experience

Data from Long-Term Observational Study

Study AI463080 was a randomized, global, observational, open-label Phase 4 study to assess long-term risks and benefits of BARACLUDE (0.5 mg/day or 1 mg/day) treatment as compared to other standard-of-care HBV nucleos(t)ide analogues in subjects with chronic HBV infection.

A total of 12,378 patients were treated with BARACLUDE (n=6,216) or other HBV nucleos(t)ide treatment [non-entecavir (ETV)] (n=6,162). Patients were evaluated at baseline and subsequently every 6 months for up to 10 years. The principal clinical outcome events assessed during the study were overall malignant neoplasms, liver-related HBV disease progression, HCC, non-HCC malignant neoplasms, and death. The study showed that BARACLUDE was not significantly associated with an increased risk of malignant neoplasms compared to other standard-of-care HBV nucleos(t)ides, as assessed by either the composite endpoint of overall malignant neoplasms or the individual endpoint of non-HCC malignant neoplasms. The most commonly reported malignancy in both the BARACLUDE and non-ETV groups was HCC followed by gastrointestinal malignancies. The data also showed that long-term BARACLUDE use was not associated with a lower occurrence of HBV disease progression or a lower rate of death overall compared to other HBV nucleos(t)ides. The principal clinical outcome event assessments are shown in Table 6.

Table 6: Principal Analyses of Time to Adjudicated Events - Randomized Treated Subjects
 |  | Number of Subjects with Events
Endpointc |  | BARACLUDE; N=6,216 | Non-ETV; N=6,162 | Hazard Ratio; [BARACLUDE:Non-ETV] (CIa)
Primary Endpoints
Overall malignant neoplasm |  | 331 | 337 | 0.93 (0.800, 1.084)
Liver-related HBV disease progression |  | 350 | 375 | 0.89 (0.769, 1.030)
Death |  | 238 | 264 | 0.85 (0.713, 1.012)
Secondary Endpoints
Non-HCC malignant neoplasm |  | 95 | 81 | 1.10 (0.817, 1.478)
HCC |  | 240b | 263 | 0.87 (0.727, 1.032)
Analyses were stratified by geographic region and prior HBV nucleos(t)ide experience.
a 95.03% CI for overall malignant neoplasm, death, and liver-related HBV disease progression; 95% CI for non-HCC malignant neoplasm and HCC.
b One subject had a pre-treatment HCC event and was excluded from the analysis.
c Overall malignant neoplasm is a composite event of HCC or non-HCC malignant neoplasm. Liver-related HBV disease progression is a composite event of liver-related death, HCC, or non-HCC HBV disease progression.
CI = confidence interval; N = total number of subjects.

Limitations of the study included population changes over the long-term follow-up period and more frequent post-randomization treatment changes in the non-ETV group. In addition, the study was underpowered to demonstrate a difference in the non-HCC malignancy rate because of the lower than expected background rate.

Adverse Reactions from Postmarketing Spontaneous Reports

The following adverse reactions have been reported during postmarketing use of BARACLUDE. Because these reactions were reported voluntarily from a population of unknown size, it is not possible to reliably estimate their frequency or establish a causal relationship to BARACLUDE exposure.

Immune system disorders: Anaphylactoid reaction.

Metabolism and nutrition disorders: Lactic acidosis.

Hepatobiliary disorders: Increased transaminases.

Skin and subcutaneous tissue disorders: Alopecia, rash.

7 DRUG INTERACTIONS

Since entecavir is primarily eliminated by the kidneys [see Clinical Pharmacology (12.3)], coadministration of BARACLUDE with drugs that reduce renal function or compete for active tubular secretion may increase serum concentrations of either entecavir or the coadministered drug. Coadministration of entecavir with lamivudine, adefovir dipivoxil, or tenofovir disoproxil fumarate did not result in significant drug interactions. The effects of coadministration of BARACLUDE with other drugs that are renally eliminated or are known to affect renal function have not been evaluated, and patients should be monitored closely for adverse events when BARACLUDE is coadministered with such drugs.

8 USE IN SPECIFIC POPULATIONS

8.1 Pregnancy

Pregnancy Exposure Registry

There is a pregnancy exposure registry that monitors pregnancy outcomes in women exposed to BARACLUDE during pregnancy. Healthcare providers are encouraged to register patients by calling the Antiretroviral Pregnancy Registry (APR) at 1-800-258-4263.

Risk Summary

Prospective pregnancy data from the APR are not sufficient to adequately assess the risk of birth defects, miscarriage or adverse maternal or fetal outcomes. Entecavir use during pregnancy has been evaluated in a limited number of individuals reported to the APR and the number of exposures to entecavir is insufficient to make a risk assessment compared to a reference population. The estimated background rate for major birth defects is 2.7% in the U.S. reference population of the Metropolitan Atlanta Congenital Defects Program (MACDP). The rate of miscarriage is not reported in the APR. All pregnancies have a background risk of birth defect, loss, or other adverse outcomes. In the U.S. general population, the estimated background risk of miscarriage in clinically recognized pregnancies is 15–20%.

In animal reproduction studies, no adverse developmental effects were observed with entecavir at clinically relevant exposures. No developmental toxicities were observed at systemic exposures (AUC) approximately 25 (rats) and 200 (rabbits) times the exposure at the maximum recommended human dose (MRHD) of 1 mg/day (see Data).

Data

Animal Data

Entecavir was administered orally to pregnant rats (at 2, 20, and 200 mg per kg per day) and rabbits (at 1, 4, and 16 mg per kg per day) during organogenesis (on gestation Days 6 through 15 [rat] and 6 through 18 [rabbit]). In rats, embryofetal toxicity including post-implantation loss, resorptions, tail and vertebral malformations, skeletal variations including reduced ossification (vertebrate, sternebrae, and phalanges) and extra lumbar vertebrae and ribs, and lower fetal body weights were observed at systemic exposures (AUC) 3,100 times those in humans at the MRHD. Maternal toxicity was also observed at this dose level. In rabbits, embryofetal toxicity including post-implantation loss, resorptions and skeletal variations, including reduced ossification (hyoid) and increased incidence of 13th rib, were observed at systemic exposures (AUC) 883 times those in humans at the MRHD. There were no signs of embryofetal toxicity when pregnant animals received oral entecavir at 28 (rat) and 212 (rabbit) times the human exposure (AUC) at the MRHD. In a pre/postnatal development study, entecavir was administered orally to pregnant rats at 0.3, 3, and 30 mg per kg per day from gestation day 6 to lactation/post-partum day 20. No adverse effects on the offspring occurred at up to the highest dose evaluated, resulting in exposures (AUC) greater than 94 times those in humans at the MRHD.

8.2 Lactation

Risk Summary

It is not known whether BARACLUDE is present in human breast milk, affects human milk production, or has effects on the breastfed infant. When administered to lactating rats, entecavir was present in milk (see Data). The developmental and health benefits of breastfeeding should be considered along with the mother’s clinical need for BARACLUDE and any potential adverse effects on the breastfed infant from BARACLUDE or from the underlying maternal condition.

Data

Entecavir was excreted into the milk of lactating rats following a single oral dose of 10 mg per kg on lactation day 7. Entecavir in milk was approximately 25% that in maternal plasma (based on AUC).

8.4 Pediatric Use

BARACLUDE was evaluated in two clinical trials of pediatric subjects 2 years of age and older with HBeAg-positive chronic HBV infection and compensated liver disease. The exposure of BARACLUDE in nucleoside-inhibitor-treatment-naïve and lamivudine-experienced pediatric subjects 2 years of age and older with HBeAg-positive chronic HBV infection and compensated liver disease receiving 0.015 mg/kg (up to 0.5 mg once daily) or 0.03 mg/kg (up to 1 mg once daily), respectively, was evaluated in Study AI463028. Safety and efficacy of the selected dose in treatment-naïve pediatric subjects were confirmed in Study AI463189, a randomized, placebo-controlled treatment trial [see Indications and Usage (1), Dosage and Administration (2.3), Adverse Reactions (6.1), Clinical Pharmacology (12.3), and Clinical Studies (14.2)].

There are limited data available on the use of BARACLUDE in lamivudine-experienced pediatric patients; BARACLUDE should be used in these patients only if the potential benefit justifies the potential risk to the child. Since some pediatric patients may require long-term or even lifetime management of chronic active hepatitis B, consideration should be given to the impact of BARACLUDE on future treatment options [see Microbiology (12.4)].

The efficacy and safety of BARACLUDE have not been established in patients less than 2 years of age. Use of BARACLUDE in this age group has not been evaluated because treatment of HBV in this age group is rarely required.

8.5 Geriatric Use

Clinical studies of BARACLUDE did not include sufficient numbers of subjects aged 65 years and over to determine whether they respond differently from younger subjects. Entecavir is substantially excreted by the kidney, and the risk of toxic reactions to this drug may be greater in patients with impaired renal function. Because elderly patients are more likely to have decreased renal function, care should be taken in dose selection, and it may be useful to monitor renal function [see Dosage and Administration (2.4)].

8.6 Racial/Ethnic Groups

There are no significant racial differences in entecavir pharmacokinetics. The safety and efficacy of BARACLUDE 0.5 mg once daily were assessed in a single-arm, open-label trial of HBeAg-positive or -negative, nucleoside-inhibitor-naïve, Black/African American (n=40) and Hispanic (n=6) subjects with chronic HBV infection. In this trial, 76% of subjects were male, the mean age was 42 years, 57% were HBeAg-positive, the mean baseline HBV DNA was 7.0 log10 IU/mL, and the mean baseline ALT was 162 U/L. At Week 48 of treatment, 32 of 46 (70%) subjects had HBV DNA <50 IU/mL (approximately 300 copies/mL), 31 of 46 (67%) subjects had ALT normalization (≤1 × ULN), and 12 of 26 (46%) HBeAg-positive subjects had HBe seroconversion. Safety data were similar to those observed in the larger controlled clinical trials.

Because of low enrollment, safety and efficacy have not been established in the US Hispanic population.

8.7 Renal Impairment

Dosage adjustment of BARACLUDE is recommended for patients with creatinine clearance less than 50 mL/min, including patients on hemodialysis or CAPD [see Dosage and Administration (2.4) and Clinical Pharmacology (12.3)].

8.8 Liver Transplant Recipients

The safety and efficacy of BARACLUDE were assessed in a single-arm, open-label trial in 65 subjects who received a liver transplant for complications of chronic HBV infection. Eligible subjects who had HBV DNA less than 172 IU/mL (approximately 1000 copies/mL) at the time of transplant were treated with BARACLUDE 1 mg once daily in addition to usual post-transplantation management, including hepatitis B immune globulin. The trial population was 82% male, 39% Caucasian, and 37% Asian, with a mean age of 49 years; 89% of subjects had HBeAg-negative disease at the time of transplant.

Four of the 65 subjects received 4 weeks or less of BARACLUDE (2 deaths, 1 re-transplantation, and 1 protocol violation) and were not considered evaluable. Of the 61 subjects who received more than 4 weeks of BARACLUDE, 60 received hepatitis B immune globulin post-transplant. Fifty-three subjects (82% of all 65 subjects treated) completed the trial and had HBV DNA measurements at or after 72 weeks treatment post-transplant. All 53 subjects had HBV DNA <50 IU/mL (approximately 300 copies/mL). Eight evaluable subjects did not have HBV DNA data available at 72 weeks, including 3 subjects who died prior to study completion. No subjects had HBV DNA values ≥50 IU/mL while receiving BARACLUDE (plus hepatitis B immune globulin). All 61 evaluable subjects lost HBsAg post-transplant; 2 of these subjects experienced recurrence of measurable HBsAg without recurrence of HBV viremia. This trial was not designed to determine whether addition of BARACLUDE to hepatitis B immune globulin decreased the proportion of subjects with measurable HBV DNA post-transplant compared to hepatitis B immune globulin alone.

If BARACLUDE treatment is determined to be necessary for a liver transplant recipient who has received or is receiving an immunosuppressant that may affect renal function, such as cyclosporine or tacrolimus, renal function must be carefully monitored both before and during treatment with BARACLUDE [see Dosage and Administration (2.4) and Clinical Pharmacology (12.3)].

10 OVERDOSAGE

There is limited experience of entecavir overdosage reported in patients. Healthy subjects who received single entecavir doses up to 40 mg or multiple doses up to 20 mg/day for up to 14 days had no increase in or unexpected adverse events. If overdose occurs, the patient must be monitored for evidence of toxicity, and standard supportive treatment applied as necessary.

Following a single 1 mg dose of entecavir, a 4-hour hemodialysis session removed approximately 13% of the entecavir dose.

11 DESCRIPTION

BARACLUDE® is the tradename for entecavir, a guanosine nucleoside analogue with selective activity against HBV. The chemical name for entecavir is 2-amino-1,9-dihydro-9-[(1S,3R,4S)-4-hydroxy-3-(hydroxymethyl)-2-methylenecyclopentyl]-6H-purin-6-one, monohydrate. Its molecular formula is C12H15N5O3•H2O, which corresponds to a molecular weight of 295.3. Entecavir has the following structural formula:

Entecavir is a white to off-white powder. It is slightly soluble in water (2.4 mg/mL), and the pH of the saturated solution in water is 7.9 at 25° C ± 0.5° C.

BARACLUDE film-coated tablets are available for oral administration in strengths of 0.5 mg and 1 mg of entecavir. BARACLUDE 0.5 mg and 1 mg film-coated tablets contain the following inactive ingredients: lactose monohydrate, microcrystalline cellulose, crospovidone, povidone, and magnesium stearate. The tablet coating contains titanium dioxide, hypromellose, polyethylene glycol 400, polysorbate 80 (0.5 mg tablet only), and iron oxide red (1 mg tablet only). BARACLUDE Oral Solution is available for oral administration as a ready-to-use solution containing 0.05 mg of entecavir per milliliter. BARACLUDE Oral Solution contains the following inactive ingredients: maltitol, sodium citrate, citric acid, methylparaben, propylparaben, and orange flavor.

12 CLINICAL PHARMACOLOGY

12.1 Mechanism of Action

Entecavir is an antiviral drug against hepatitis B virus [see Microbiology (12.4)].

12.3 Pharmacokinetics

The single- and multiple-dose pharmacokinetics of entecavir were evaluated in healthy subjects and subjects with chronic hepatitis B virus infection.

Absorption

Following oral administration in healthy subjects, entecavir peak plasma concentrations occurred between 0.5 and 1.5 hours. Following multiple daily doses ranging from 0.1 to 1 mg, Cmax and area under the concentration-time curve (AUC) at steady state increased in proportion to dose. Steady state was achieved after 6 to 10 days of once-daily administration with approximately 2-fold accumulation. For a 0.5 mg oral dose, Cmax at steady state was 4.2 ng/mL and trough plasma concentration (Ctrough) was 0.3 ng/mL. For a 1 mg oral dose, Cmax was 8.2 ng/mL and Ctrough was 0.5 ng/mL.

In healthy subjects, the bioavailability of the tablet was 100% relative to the oral solution. The oral solution and tablet may be used interchangeably.

Effects of food on oral absorption: Oral administration of 0.5 mg of entecavir with a standard high-fat meal (945 kcal, 54.6 g fat) or a light meal (379 kcal, 8.2 g fat) resulted in a delay in absorption (1.0–1.5 hours fed vs. 0.75 hours fasted), a decrease in Cmax of 44%–46%, and a decrease in AUC of 18%–20% [see Dosage and Administration (2)].

Distribution

Based on the pharmacokinetic profile of entecavir after oral dosing, the estimated apparent volume of distribution is in excess of total body water, suggesting that entecavir is extensively distributed into tissues.

Binding of entecavir to human serum proteins in vitro was approximately 13%.

Metabolism and Elimination

Following administration of ^14C-entecavir in humans and rats, no oxidative or acetylated metabolites were observed. Minor amounts of phase II metabolites (glucuronide and sulfate conjugates) were observed. Entecavir is not a substrate, inhibitor, or inducer of the cytochrome P450 (CYP450) enzyme system. See Drug Interactions, below.

After reaching peak concentration, entecavir plasma concentrations decreased in a bi-exponential manner with a terminal elimination half-life of approximately 128–149 hours. The observed drug accumulation index is approximately 2-fold with once-daily dosing, suggesting an effective accumulation half-life of approximately 24 hours.

Entecavir is predominantly eliminated by the kidney with urinary recovery of unchanged drug at steady state ranging from 62% to 73% of the administered dose. Renal clearance is independent of dose and ranges from 360 to 471 mL/min suggesting that entecavir undergoes both glomerular filtration and net tubular secretion [see Drug Interactions (7)].

Special Populations

Gender: There are no significant gender differences in entecavir pharmacokinetics.

Race: There are no significant racial differences in entecavir pharmacokinetics.

Elderly: The effect of age on the pharmacokinetics of entecavir was evaluated following administration of a single 1 mg oral dose in healthy young and elderly volunteers. Entecavir AUC was 29.3% greater in elderly subjects compared to young subjects. The disparity in exposure between elderly and young subjects was most likely attributable to differences in renal function. Dosage adjustment of BARACLUDE should be based on the renal function of the patient, rather than age [see Dosage and Administration (2.4)].

Pediatrics: The steady-state pharmacokinetics of entecavir were evaluated in nucleoside-inhibitor-naïve and lamivudine-experienced HBeAg-positive pediatric subjects 2 to less than 18 years of age with compensated liver disease. Results are shown in Table 7. Entecavir exposure among nucleoside-inhibitor-naïve subjects was similar to the exposure achieved in adults receiving once-daily doses of 0.5 mg. Entecavir exposure among lamivudine-experienced subjects was similar to the exposure achieved in adults receiving once-daily doses of 1 mg.

Table 7: Pharmacokinetic Parameters in Pediatric Subjects
 | Nucleoside-Inhibitor‑Naïvea | Lamivudine‑Experiencedb
 | n=24 | n=19
Cmax (ng/mL) (CV%) | 6.31 (30) | 14.48 (31)
AUC(0–24) (ng•h/mL) (CV%) | 18.33 (27) | 38.58 (26)
Cmin (ng/mL) (CV%) | 0.28 (22) | 0.47 (23)
a Subjects received once-daily doses of 0.015 mg/kg up to a maximum of 0.5 mg.
b Subjects received once-daily doses of 0.030 mg/kg up to a maximum of 1 mg.

Renal impairment: The pharmacokinetics of entecavir following a single 1 mg dose were studied in subjects (without chronic hepatitis B virus infection) with selected degrees of renal impairment, including subjects whose renal impairment was managed by hemodialysis or continuous ambulatory peritoneal dialysis (CAPD). Results are shown in Table 8 [see Dosage and Administration (2.4)].

Table 8: Pharmacokinetic Parameters in Subjects with Selected Degrees of Renal Function
 | Renal Function Group
 | Baseline Creatinine Clearance (mL/min)
 | Unimpaired; >80 | Mild; >50–≤80 | Moderate; 30–50 | Severe; <30 | Severe; Managed with; Hemodialysisa | Severe; Managed; with CAPD
 | n=6 | n=6 | n=6 | n=6 | n=6 | n=4
Cmax (ng/mL); (CV%) | 8.1; (30.7) | 10.4; (37.2) | 10.5; (22.7) | 15.3; (33.8) | 15.4; (56.4) | 16.6; (29.7)
AUC(0–T) (ng•h/mL); (CV) | 27.9; (25.6) | 51.5; (22.8) | 69.5; (22.7) | 145.7; (31.5) | 233.9; (28.4) | 221.8; (11.6)
CLR (mL/min); (SD) | 383.2; (101.8) | 197.9; (78.1) | 135.6; (31.6) | 40.3; (10.1) | NA | NA
CLT/F (mL/min); (SD) | 588.1; (153.7) | 309.2; (62.6) | 226.3; (60.1) | 100.6; (29.1) | 50.6; (16.5) | 35.7; (19.6)
a Dosed immediately following hemodialysis.
CLR = renal clearance; CLT/F = apparent oral clearance.

Following a single 1 mg dose of entecavir administered 2 hours before the hemodialysis session, hemodialysis removed approximately 13% of the entecavir dose over 4 hours. CAPD removed approximately 0.3% of the dose over 7 days [see Dosage and Administration (2.4)].

Hepatic impairment: The pharmacokinetics of entecavir following a single 1 mg dose were studied in adult subjects (without chronic hepatitis B virus infection) with moderate or severe hepatic impairment (Child-Turcotte-Pugh Class B or C). The pharmacokinetics of entecavir were similar between hepatically impaired and healthy control subjects; therefore, no dosage adjustment of BARACLUDE is recommended for patients with hepatic impairment. The pharmacokinetics of entecavir have not been studied in pediatric subjects with hepatic impairment.

Post-liver transplant: Limited data are available on the safety and efficacy of BARACLUDE in liver transplant recipients. In a small pilot study of entecavir use in HBV-infected liver transplant recipients on a stable dose of cyclosporine A (n=5) or tacrolimus (n=4), entecavir exposure was approximately 2-fold the exposure in healthy subjects with normal renal function. Altered renal function contributed to the increase in entecavir exposure in these subjects. The potential for pharmacokinetic interactions between entecavir and cyclosporine A or tacrolimus was not formally evaluated [see Use in Specific Populations (8.8)].

Drug Interactions

The metabolism of entecavir was evaluated in in vitro and in vivo studies. Entecavir is not a substrate, inhibitor, or inducer of the cytochrome P450 (CYP450) enzyme system. At concentrations up to approximately 10,000-fold higher than those obtained in humans, entecavir inhibited none of the major human CYP450 enzymes 1A2, 2C9, 2C19, 2D6, 3A4, 2B6, and 2E1. At concentrations up to approximately 340-fold higher than those observed in humans, entecavir did not induce the human CYP450 enzymes 1A2, 2C9, 2C19, 3A4, 3A5, and 2B6. The pharmacokinetics of entecavir are unlikely to be affected by coadministration with agents that are either metabolized by, inhibit, or induce the CYP450 system. Likewise, the pharmacokinetics of known CYP substrates are unlikely to be affected by coadministration of entecavir.

The steady-state pharmacokinetics of entecavir and coadministered drug were not altered in interaction studies of entecavir with lamivudine, adefovir dipivoxil, and tenofovir disoproxil fumarate [see Drug Interactions (7)].

12.4 Microbiology

Mechanism of Action

Entecavir, a deoxyguanosine nucleoside analogue with activity against HBV reverse transcriptase (rt), is efficiently phosphorylated to the active triphosphate form, which has an intracellular half-life of 15 hours. By competing with the natural substrate deoxyguanosine triphosphate, entecavir triphosphate functionally inhibits all three activities of the HBV reverse transcriptase: (1) base priming, (2) reverse transcription of the negative strand from the pregenomic messenger RNA, and (3) synthesis of the positive strand of HBV DNA. Entecavir triphosphate is a weak inhibitor of cellular DNA polymerases α, β, and δ and mitochondrial DNA polymerase γ with Ki values ranging from 18 to >160 µM.

Antiviral Activity

Entecavir inhibited HBV DNA synthesis (50% reduction, EC50) at a concentration of 0.004 µM in human HepG2 cells transfected with wild-type HBV. The median EC50 value for entecavir against lamivudine-resistant HBV (rtL180M, rtM204V) was 0.026 µM (range 0.010–0.059 µM).

The coadministration of HIV nucleoside/nucleotide reverse transcriptase inhibitors (NRTIs) with BARACLUDE is unlikely to reduce the antiviral efficacy of BARACLUDE against HBV or of any of these agents against HIV. In HBV combination assays in cell culture, abacavir, didanosine, lamivudine, stavudine, tenofovir, or zidovudine were not antagonistic to the anti-HBV activity of entecavir over a wide range of concentrations. In HIV antiviral assays, entecavir was not antagonistic to the cell culture anti-HIV activity of these six NRTIs or emtricitabine at concentrations greater than 100 times the Cmax of entecavir using the 1 mg dose.

Antiviral Activity Against HIV

A comprehensive analysis of the inhibitory activity of entecavir against a panel of laboratory and clinical HIV type 1 (HIV-1) isolates using a variety of cells and assay conditions yielded EC50 values ranging from 0.026 to >10 µM; the lower EC50 values were observed when decreased levels of virus were used in the assay. In cell culture, entecavir selected for an M184I substitution in HIV reverse transcriptase at micromolar concentrations, confirming inhibitory pressure at high entecavir concentrations. HIV variants containing the M184V substitution showed loss of susceptibility to entecavir.

Resistance

In Cell Culture

In cell-based assays, 8- to 30-fold reductions in entecavir phenotypic susceptibility were observed for lamivudine-resistant strains. Further reductions (>70-fold) in entecavir phenotypic susceptibility required the presence of amino acid substitutions rtM204I/V with or without rtL180M along with additional substitutions at residues rtT184, rtS202, or rtM250, or a combination of these substitutions with or without an rtI169 substitution in the HBV reverse transcriptase. Lamivudine-resistant strains harboring rtL180M plus rtM204V in combination with the amino acid substitution rtA181C conferred 16- to 122-fold reductions in entecavir phenotypic susceptibility.

Clinical Studies

Nucleoside-inhibitor-naïve subjects: Genotypic evaluations were performed on evaluable samples (>300 copies/mL serum HBV DNA) from 562 subjects who were treated with BARACLUDE for up to 96 weeks in nucleoside-inhibitor-naïve studies (AI463022, AI463027, and rollover study AI463901). By Week 96, evidence of emerging amino acid substitution rtS202G with rtL180M and rtM204V substitutions was detected in the HBV of 2 subjects (2/562=<1%), and 1 of them experienced virologic rebound (≥1 log10 increase above nadir). In addition, emerging amino acid substitutions at rtM204I/V and rtL80I, rtV173L, or rtL180M, which conferred decreased phenotypic susceptibility to entecavir in the absence of rtT184, rtS202, or rtM250 changes, were detected in the HBV of 3 subjects (3/562=<1%) who experienced virologic rebound. For subjects who continued treatment beyond 48 weeks, 75% (202/269) had HBV DNA <300 copies/mL at end of dosing (up to 96 weeks).

HBeAg-positive (n=243) and -negative (n=39) treatment-naïve subjects who failed to achieve the study-defined complete response by 96 weeks were offered continued entecavir treatment in a rollover study. Complete response for HBeAg-positive was <0.7 MEq/mL (approximately 7 × 10^5 copies/mL) serum HBV DNA and HBeAg loss and, for HBeAg-negative was <0.7 MEq/mL HBV DNA and ALT normalization. Subjects received 1 mg entecavir once daily for up to an additional 144 weeks. Of these 282 subjects, 141 HBeAg-positive and 8 HBeAg-negative subjects entered the long-term follow-up rollover study and were evaluated for entecavir resistance. Of the 149 subjects entering the rollover study, 88% (131/149), 92% (137/149), and 92% (137/149) attained serum HBV DNA <300 copies/mL by Weeks 144, 192, and 240 (including end of dosing), respectively. No novel entecavir resistance-associated substitutions were identified in a comparison of the genotypes of evaluable isolates with their respective baseline isolates. The cumulative probability of developing rtT184, rtS202, or rtM250 entecavir resistance-associated substitutions (in the presence of rtL180M and rtM204V substitutions) at Weeks 48, 96, 144, 192, and 240 was 0.2%, 0.5%, 1.2%, 1.2%, and 1.2%, respectively.

Lamivudine-refractory subjects: Genotypic evaluations were performed on evaluable samples from 190 subjects treated with BARACLUDE for up to 96 weeks in studies of lamivudine-refractory HBV (AI463026, AI463014, AI463015, and rollover study AI463901). By Week 96, resistance-associated amino acid substitutions at rtT184, rtS202, or rtM250, with or without rtI169 changes, in the presence of amino acid substitutions rtM204I/V with or without rtL80V, rtV173L/M, or rtL180M emerged in the HBV from 22 subjects (22/190=12%), 16 of whom experienced virologic rebound (≥1 log10 increase above nadir) and 4 of whom were never suppressed <300 copies/mL. The HBV from 4 of these subjects had entecavir resistance substitutions at baseline and acquired further changes on entecavir treatment. In addition to the 22 subjects, 3 subjects experienced virologic rebound with the emergence of rtM204I/V and rtL80V, rtV173L/M, or rtL180M. For isolates from subjects who experienced virologic rebound with the emergence of resistance-associated substitutions (n=19), the median fold-change in entecavir EC50 values from reference was 19-fold at baseline and 106-fold at the time of virologic rebound. For subjects who continued treatment beyond 48 weeks, 40% (31/77) had HBV DNA <300 copies/mL at end of dosing (up to 96 weeks).

Lamivudine-refractory subjects (n=157) who failed to achieve the study-defined complete response by Week 96 were offered continued entecavir treatment. Subjects received 1 mg entecavir once daily for up to an additional 144 weeks. Of these subjects, 80 subjects entered the long-term follow-up study and were evaluated for entecavir resistance. By Weeks 144, 192, and 240 (including end of dosing), 34% (27/80), 35% (28/80), and 36% (29/80), respectively, attained HBV DNA <300 copies/mL. The cumulative probability of developing rtT184, rtS202, or rtM250 entecavir resistance-associated substitutions (in the presence of rtM204I/V with or without rtL180M substitutions) at Weeks 48, 96, 144, 192, and 240 was 6.2%, 15%, 36.3%, 46.6%, and 51.5%, respectively. The HBV of 6 subjects developed rtA181C/G/S/T amino acid substitutions while receiving entecavir, and of these, 4 developed entecavir resistance-associated substitutions at rtT184, rtS202, or rtM250 and 1 had an rtT184S substitution at baseline. Of 7 subjects whose HBV had an rtA181 substitution at baseline, 2 also had substitutions at rtT184, rtS202, or rtM250 at baseline and another 2 developed them while on treatment with entecavir.

In a post-approval integrated analysis of entecavir resistance data from 17 Phase 2 and 3 clinical trials, an emergent entecavir resistance-associated substitution rtA181C was detected in 5 out of 1461 (0.3%) subjects during treatment with entecavir. This substitution was detected only in the presence of lamivudine resistance-associated substitutions rtL180M plus rtM204V.

Cross-resistance

Cross-resistance has been observed among HBV nucleoside analogue inhibitors. In cell-based assays, entecavir had 8- to 30-fold less inhibition of HBV DNA synthesis for HBV containing lamivudine and telbivudine resistance-associated substitutions rtM204I/V with or without rtL180M than for wild-type HBV. Substitutions rtM204I/V with or without rtL80I/V, rtV173L, or rtL180M, which are associated with lamivudine and telbivudine resistance, also confer decreased phenotypic susceptibility to entecavir. The efficacy of entecavir against HBV harboring adefovir resistance-associated substitutions has not been established in clinical trials. HBV isolates from lamivudine-refractory subjects failing entecavir therapy were susceptible in cell culture to adefovir but remained resistant to lamivudine. Recombinant HBV genomes encoding adefovir resistance-associated substitutions at either rtA181V or rtN236T had 1.1- or 0.3-fold shifts in susceptibility to entecavir in cell culture, respectively.

13 NONCLINICAL TOXICOLOGY

13.1 Carcinogenesis, Mutagenesis, Impairment of Fertility

Carcinogenesis

Long-term oral carcinogenicity studies of entecavir in mice and rats were carried out at exposures up to approximately 42 times (mice) and 35 times (rats) those observed in humans at the highest recommended dose of 1 mg/day. In mouse and rat studies, entecavir was positive for carcinogenic findings. It is not known how predictive the results of rodent carcinogenicity studies may be for humans [see Adverse Reactions (6.2)].

In mice, lung adenomas were increased in males and females at exposures 3 and 40 times those in humans. Lung carcinomas in both male and female mice were increased at exposures 40 times those in humans. Combined lung adenomas and carcinomas were increased in male mice at exposures 3 times and in female mice at exposures 40 times those in humans. Tumor development was preceded by pneumocyte proliferation in the lung, which was not observed in rats, dogs, or monkeys administered entecavir, supporting the conclusion that lung tumors in mice may be a species-specific event. Hepatocellular carcinomas were increased in males and combined liver adenomas and carcinomas were also increased at exposures 42 times those in humans. Vascular tumors in female mice (hemangiomas of ovaries and uterus and hemangiosarcomas of spleen) were increased at exposures 40 times those in humans. In rats, hepatocellular adenomas were increased in females at exposures 24 times those in humans; combined adenomas and carcinomas were also increased in females at exposures 24 times those in humans. Brain gliomas were induced in both males and females at exposures 35 and 24 times those in humans. Skin fibromas were induced in females at exposures 4 times those in humans.

Mutagenesis

Entecavir was clastogenic to human lymphocyte cultures. Entecavir was not mutagenic in the Ames bacterial reverse mutation assay using S. typhimurium and E. coli strains in the presence or absence of metabolic activation, a mammalian-cell gene mutation assay, and a transformation assay with Syrian hamster embryo cells. Entecavir was also negative in an oral micronucleus study and an oral DNA repair study in rats.

Impairment of Fertility

In reproductive toxicology studies, in which animals were administered entecavir at up to 30 mg/kg for up to 4 weeks, no evidence of impaired fertility was seen in male or female rats at systemic exposures greater than 90 times those achieved in humans at the highest recommended dose of 1 mg/day. In rodent and dog toxicology studies, seminiferous tubular degeneration was observed at exposures 35 times or greater than those achieved in humans. No testicular changes were evident in monkeys.

14 CLINICAL STUDIES

14.1 Outcomes in Adults

At 48 Weeks

The safety and efficacy of BARACLUDE in adults were evaluated in three Phase 3 active-controlled trials. These studies included 1633 subjects 16 years of age or older with chronic hepatitis B virus infection (serum HBsAg-positive for at least 6 months) accompanied by evidence of viral replication (detectable serum HBV DNA, as measured by the bDNA hybridization or PCR assay). Subjects had persistently elevated ALT levels at least 1.3 times ULN and chronic inflammation on liver biopsy compatible with a diagnosis of chronic viral hepatitis. The safety and efficacy of BARACLUDE were also evaluated in a study of 191 HBV-infected subjects with decompensated liver disease and in a study of 68 subjects co-infected with HBV and HIV.

Nucleoside-inhibitor-naïve Subjects with Compensated Liver Disease

HBeAg-positive: Study AI463022 was a multinational, randomized, double-blind study of BARACLUDE 0.5 mg once daily versus lamivudine 100 mg once daily for a minimum of 52 weeks in 709 (of 715 randomized) nucleoside-inhibitor-naïve subjects with chronic hepatitis B virus infection, compensated liver disease, and detectable HBeAg. The mean age of subjects was 35 years, 75% were male, 57% were Asian, 40% were Caucasian, and 13% had previously received interferon-α. At baseline, subjects had a mean Knodell Necroinflammatory Score of 7.8, mean serum HBV DNA as measured by Roche COBAS Amplicor® PCR assay was 9.66 log10 copies/mL, and mean serum ALT level was 143 U/L. Paired, adequate liver biopsy samples were available for 89% of subjects.

HBeAg-negative (anti-HBe-positive/HBV DNA-positive): Study AI463027 was a multinational, randomized, double-blind study of BARACLUDE 0.5 mg once daily versus lamivudine 100 mg once daily for a minimum of 52 weeks in 638 (of 648 randomized) nucleoside-inhibitor-naïve subjects with HBeAg-negative (HBeAb-positive) chronic hepatitis B virus infection and compensated liver disease. The mean age of subjects was 44 years, 76% were male, 39% were Asian, 58% were Caucasian, and 13% had previously received interferon-α. At baseline, subjects had a mean Knodell Necroinflammatory Score of 7.8, mean serum HBV DNA as measured by Roche COBAS Amplicor PCR assay was 7.58 log10 copies/mL, and mean serum ALT level was 142 U/L. Paired, adequate liver biopsy samples were available for 88% of subjects.

In Studies AI463022 and AI463027, BARACLUDE was superior to lamivudine on the primary efficacy endpoint of Histologic Improvement, defined as a 2-point or greater reduction in Knodell Necroinflammatory Score with no worsening in Knodell Fibrosis Score at Week 48, and on the secondary efficacy measures of reduction in viral load and ALT normalization. Histologic Improvement and change in Ishak Fibrosis Score are shown in Table 9. Selected virologic, biochemical, and serologic outcome measures are shown in Table 10.

Table 9: Histologic Improvement and Change in Ishak Fibrosis Score at Week 48, Nucleoside-Inhibitor-Naïve Subjects in Studies AI463022 and AI463027

 | Study AI463022 (HBeAg-Positive) |  | Study AI463027 (HBeAg-Negative)
 | BARACLUDE; 0.5 mg; n=314a | Lamivudine; 100 mg; n=314a | BARACLUDE; 0.5 mg; n=296a | Lamivudine; 100 mg; n=287a
Histologic Improvement
(Knodell Scores)
Improvementb | 72% | 62% | 70% | 61%
No improvement | 21% | 24% | 19% | 26%
Ishak Fibrosis Score
Improvementc | 39% | 35% | 36% | 38%
No change | 46% | 40% | 41% | 34%
Worseningc | 8% | 10% | 12% | 15%
Missing Week 48 biopsy | 7% | 14% | 10% | 13%
a Subjects with evaluable baseline histology (baseline Knodell Necroinflammatory Score ≥2).
b ≥2-point decrease in Knodell Necroinflammatory Score from baseline with no worsening of the Knodell Fibrosis Score.
c For Ishak Fibrosis Score, improvement = ≥1-point decrease from baseline and worsening = ≥1-point increase from baseline.

Table 10: Selected Virologic, Biochemical, and Serologic Endpoints at Week 48, Nucleoside-Inhibitor-Naïve Subjects in Studies AI463022 and AI463027
 | Study AI463022; (HBeAg-Positive) |  | Study AI463027; (HBeAg-Negative)
 | BARACLUDE; 0.5 mg; n=354 | Lamivudine; 100 mg; n=355 | BARACLUDE; 0.5 mg; n=325 | Lamivudine; 100 mg; n=313
HBV DNAa
Proportion undetectable (<300 copies/mL) | 67% | 36% | 90% | 72%
Mean change from baseline; (log10 copies/mL) | ‑6.86 | ‑5.39 | ‑5.04 | ‑4.53
ALT normalization (≤1 × ULN) | 68% | 60% | 78% | 71%
HBeAg seroconversion | 21% | 18% | NA | NA
a Roche COBAS Amplicor PCR assay [lower limit of quantification (LLOQ) = 300 copies/mL].

Histologic Improvement was independent of baseline levels of HBV DNA or ALT.

Lamivudine-refractory Subjects with Compensated Liver Disease

Study AI463026 was a multinational, randomized, double-blind study of BARACLUDE in 286 (of 293 randomized) subjects with lamivudine-refractory chronic hepatitis B virus infection and compensated liver disease. Subjects receiving lamivudine at study entry either switched to BARACLUDE 1 mg once daily (with neither a washout nor an overlap period) or continued on lamivudine 100 mg for a minimum of 52 weeks. The mean age of subjects was 39 years, 76% were male, 37% were Asian, 62% were Caucasian, and 52% had previously received interferon-α. The mean duration of prior lamivudine therapy was 2.7 years, and 85% had lamivudine resistance substitutions at baseline by an investigational line probe assay. At baseline, subjects had a mean Knodell Necroinflammatory Score of 6.5, mean serum HBV DNA as measured by Roche COBAS Amplicor PCR assay was 9.36 log10 copies/mL, and mean serum ALT level was 128 U/L. Paired, adequate liver biopsy samples were available for 87% of subjects.

BARACLUDE was superior to lamivudine on a primary endpoint of Histologic Improvement (using the Knodell Score at Week 48). These results and change in Ishak Fibrosis Score are shown in Table 11. Table 12 shows selected virologic, biochemical, and serologic endpoints.

Table 11: Histologic Improvement and Change in Ishak Fibrosis Score at Week 48, Lamivudine-Refractory Subjects in Study AI463026
 | BARACLUDE; 1 mg; n=124a | Lamivudine; 100 mg; n=116a
Histologic Improvement (Knodell Scores)
Improvementb | 55% | 28%
No improvement | 34% | 57%
Ishak Fibrosis Score
Improvementc | 34% | 16%
No change | 44% | 42%
Worseningc | 11% | 26%
Missing Week 48 biopsy | 11% | 16%
a Subjects with evaluable baseline histology (baseline Knodell Necroinflammatory Score ≥2).
b ≥2-point decrease in Knodell Necroinflammatory Score from baseline with no worsening of the Knodell Fibrosis Score.
c For Ishak Fibrosis Score, improvement = ≥1-point decrease from baseline and worsening = ≥1-point increase from baseline.

Table 12: Selected Virologic, Biochemical, and Serologic Endpoints at Week 48, Lamivudine-Refractory Subjects in Study AI463026
 | BARACLUDE; 1 mg; n=141 | Lamivudine; 100 mg; n=145
HBV DNAa
Proportion undetectable (<300 copies/mL) | 19% | 1%
Mean change from baseline (log10 copies/mL) | ‑5.11 | ‑0.48
ALT normalization (≤1 × ULN) | 61% | 15%
HBeAg seroconversion | 8% | 3%
a Roche COBAS Amplicor PCR assay (LLOQ = 300 copies/mL).

Histologic Improvement was independent of baseline levels of HBV DNA or ALT.

Subjects with Decompensated Liver Disease

Study AI463048 was a randomized, open-label study of BARACLUDE 1 mg once daily versus adefovir dipivoxil 10 mg once daily in 191 (of 195 randomized) adult subjects with HBeAg-positive or -negative chronic HBV infection and evidence of hepatic decompensation, defined as a Child-Turcotte-Pugh (CTP) score of 7 or higher. Subjects were either HBV-treatment-naïve or previously treated, predominantly with lamivudine or interferon-α.

In Study AI463048, 100 subjects were randomized to treatment with BARACLUDE and 91 subjects to treatment with adefovir dipivoxil. Two subjects randomized to treatment with adefovir dipivoxil actually received treatment with BARACLUDE for the duration of the study. The mean age of subjects was 52 years, 74% were male, 54% were Asian, 33% were Caucasian, and 5% were Black/African American. At baseline, subjects had a mean serum HBV DNA by PCR of 7.83 log10 copies/mL and mean ALT level of 100 U/L; 54% of subjects were HBeAg-positive; 35% had genotypic evidence of lamivudine resistance. The baseline mean CTP score was 8.6. Results for selected study endpoints at Week 48 are shown in Table 13.

Table 13: Selected Endpoints at Week 48, Subjects with Decompensated Liver Disease, Study AI463048
 | BARACLUDE; 1 mg; n=100a | Adefovir Dipivoxil; 10 mg; n=91a
HBV DNAb
Proportion undetectable (<300 copies/mL) | 57% | 20%
Stable or improved CTP scorec | 61% | 67%
HBsAg loss | 5% | 0
Normalization of ALT (≤1 × ULN)d | 49/78 (63%) | 33/71 (46%)
a Endpoints were analyzed using intention-to-treat (ITT) method, treated subjects as randomized.
b Roche COBAS Amplicor PCR assay (LLOQ = 300 copies/mL).
c Defined as decrease or no change from baseline in CTP score.
d Denominator is subjects with abnormal values at baseline.
ULN=upper limit of normal.

Subjects Co-infected with HIV and HBV

Study AI463038 was a randomized, double-blind, placebo-controlled study of BARACLUDE versus placebo in 68 subjects co-infected with HIV and HBV who experienced recurrence of HBV viremia while receiving a lamivudine-containing highly active antiretroviral (HAART) regimen. Subjects continued their lamivudine-containing HAART regimen (lamivudine dose 300 mg/day) and were assigned to add either BARACLUDE 1 mg once daily (51 subjects) or placebo (17 subjects) for 24 weeks followed by an open-label phase for an additional 24 weeks where all subjects received BARACLUDE. At baseline, subjects had a mean serum HBV DNA level by PCR of 9.13 log10 copies/mL. Ninety-nine percent of subjects were HBeAg-positive at baseline, with a mean baseline ALT level of 71.5 U/L. Median HIV RNA level remained stable at approximately 2 log10 copies/mL through 24 weeks of blinded therapy. Virologic and biochemical endpoints at Week 24 are shown in Table 14. There are no data in patients with HIV/HBV co-infection who have not received prior lamivudine therapy. BARACLUDE has not been evaluated in HIV/HBV co-infected patients who were not simultaneously receiving effective HIV treatment [see Warnings and Precautions (5.2)].

Table 14: Virologic and Biochemical Endpoints at Week 24, Study AI463038

 | BARACLUDE 1 mga; n=51 | Placeboa; n=17
HBV DNAb
Proportion undetectable (<300 copies/mL) | 6% | 0
Mean change from baseline (log10 copies/mL) | ‑3.65 | +0.11
ALT normalization (≤1 × ULN) | 34%c | 8%c
a All subjects also received a lamivudine-containing HAART regimen.
b Roche COBAS Amplicor PCR assay (LLOQ = 300 copies/mL).
c Percentage of subjects with abnormal ALT (>1 × ULN) at baseline who achieved ALT normalization (n=35 for BARACLUDE and n=12 for placebo).

For subjects originally assigned to BARACLUDE, at the end of the open-label phase (Week 48), 8% of subjects had HBV DNA <300 copies/mL by PCR, the mean change from baseline HBV DNA by PCR was −4.20 log10 copies/mL, and 37% of subjects with abnormal ALT at baseline had ALT normalization (≤1 × ULN).

Beyond 48 Weeks

The optimal duration of therapy with BARACLUDE is unknown. According to protocol-mandated criteria in the Phase 3 clinical trials, subjects discontinued BARACLUDE or lamivudine treatment after 52 weeks according to a definition of response based on HBV virologic suppression (<0.7 MEq/mL by bDNA assay) and loss of HBeAg (in HBeAg-positive subjects) or ALT <1.25 × ULN (in HBeAg-negative subjects) at Week 48. Subjects who achieved virologic suppression but did not have serologic response (HBeAg-positive) or did not achieve ALT <1.25 × ULN (HBeAg-negative) continued blinded dosing through 96 weeks or until the response criteria were met. These protocol-specified subject management guidelines are not intended as guidance for clinical practice.

Nucleoside-inhibitor-naïve Subjects

Among nucleoside-inhibitor-naïve, HBeAg-positive subjects (Study AI463022), 243 (69%) BARACLUDE-treated subjects and 164 (46%) lamivudine-treated subjects continued blinded treatment for up to 96 weeks. Of those continuing blinded treatment in Year 2, 180 (74%) BARACLUDE subjects and 60 (37%) lamivudine subjects achieved HBV DNA <300 copies/mL by PCR at the end of dosing (up to 96 weeks). 193 (79%) BARACLUDE subjects achieved ALT ≤1 × ULN compared to 112 (68%) lamivudine subjects, and HBeAg seroconversion occurred in 26 (11%) BARACLUDE subjects and 20 (12%) lamivudine subjects.

Among nucleoside-inhibitor-naïve, HBeAg-positive subjects, 74 (21%) BARACLUDE subjects and 67 (19%) lamivudine subjects met the definition of response at Week 48, discontinued study drugs, and were followed off treatment for 24 weeks. Among BARACLUDE responders, 26 (35%) subjects had HBV DNA <300 copies/mL, 55 (74%) subjects had ALT ≤1 × ULN, and 56 (76%) subjects sustained HBeAg seroconversion at the end of follow-up. Among lamivudine responders, 20 (30%) subjects had HBV DNA <300 copies/mL, 41 (61%) subjects had ALT ≤1 × ULN, and 47 (70%) subjects sustained HBeAg seroconversion at the end of follow-up.

Among nucleoside-inhibitor-naïve, HBeAg-negative subjects (Study AI463027), 26 (8%) BARACLUDE-treated subjects and 28 (9%) lamivudine-treated subjects continued blinded treatment for up to 96 weeks. In this small cohort continuing treatment in Year 2, 22 BARACLUDE and 16 lamivudine subjects had HBV DNA <300 copies/mL by PCR, and 7 and 6 subjects, respectively, had ALT ≤1 × ULN at the end of dosing (up to 96 weeks).

Among nucleoside-inhibitor-naïve, HBeAg-negative subjects, 275 (85%) BARACLUDE subjects and 245 (78%) lamivudine subjects met the definition of response at Week 48, discontinued study drugs, and were followed off treatment for 24 weeks. In this cohort, very few subjects in each treatment arm had HBV DNA <300 copies/mL by PCR at the end of follow-up. At the end of follow-up, 126 (46%) BARACLUDE subjects and 84 (34%) lamivudine subjects had ALT ≤1 × ULN.

Lamivudine-refractory Subjects

Among lamivudine-refractory subjects (Study AI463026), 77 (55%) BARACLUDE-treated subjects and 3 (2%) lamivudine subjects continued blinded treatment for up to 96 weeks. In this cohort of BARACLUDE subjects, 31 (40%) subjects achieved HBV DNA <300 copies/mL, 62 (81%) subjects had ALT ≤1 × ULN, and 8 (10%) subjects demonstrated HBeAg seroconversion at the end of dosing.

14.2 Outcomes in Pediatric Subjects

The pharmacokinetics, safety and antiviral activity of BARACLUDE in pediatric subjects were initially assessed in Study AI463028. Twenty-four treatment-naïve and 19 lamivudine-experienced HBeAg-positive pediatric subjects 2 to less than 18 years of age with compensated chronic hepatitis B virus infection and elevated ALT were treated with BARACLUDE 0.015 mg/kg (up to 0.5 mg) or 0.03 mg/kg (up to 1 mg) once daily. Fifty-eight percent (14/24) of treatment-naïve subjects and 47% (9/19) of lamivudine-experienced subjects achieved HBV DNA <50 IU/mL at Week 48 and ALT normalized in 83% (20/24) of treatment-naïve and 95% (18/19) of lamivudine-experienced subjects.

Safety and antiviral efficacy were confirmed in Study AI463189, a study of BARACLUDE among 180 nucleoside-inhibitor-treatment-naïve pediatric subjects 2 to less than 18 years of age with HBeAg-positive chronic hepatitis B infection, compensated liver disease, and elevated ALT. Subjects were randomized 2:1 to receive blinded treatment with BARACLUDE 0.015 mg/kg up to 0.5 mg/day (N=120) or placebo (N=60). The randomization was stratified by age group (2 to 6 years; >6 to 12 years; and >12 to <18 years). Baseline demographics and HBV disease characteristics were comparable between the 2 treatment arms and across age cohorts. At study entry, the mean HBV DNA was 8.1 log10 IU/mL and mean ALT was 103 U/L. The primary efficacy endpoint was a composite of HBeAg seroconversion and serum HBV DNA <50 IU/mL at Week 48 assessed in the first 123 subjects reaching 48 weeks of blinded treatment. Twenty-four percent (20/82) of subjects in the BARACLUDE-treated group and 2% (1/41) of subjects in the placebo-treated group met the primary endpoint. Forty-six percent (38/82) of BARACLUDE-treated subjects and 2% (1/41) of placebo-treated subjects achieved HBV DNA <50 IU/mL at Week 48. ALT normalization occurred in 67% (55/82) of BARACLUDE-treated subjects and 22% (9/41) of placebo-treated subjects; 24% (20/82) of BARACLUDE-treated subjects and 12% (5/41) of placebo-treated subjects had HBeAg seroconversion.

16 HOW SUPPLIED/STORAGE AND HANDLING

BARACLUDE® (entecavir) Tablets and Oral Solution are available in the following strengths and configurations of plastic bottles with child-resistant closures:

Product Strength and; Dosage Form | Description | Quantity | NDC Number
0.5 mg film-coated tablet | White to off-white, triangular-shaped tablet, debossed with “BMS” on one side and “1611” on the other side. | 30 tablets | 0003-1611-12
1 mg film-coated tablet | Pink, triangular-shaped tablet, debossed with “BMS” on one side and “1612” on the other side. | 30 tablets | 0003-1612-12
0.05 mg/mL oral solution | Ready-to-use, orange-flavored, clear, colorless to pale yellow, aqueous solution in a 260 mL bottle. | 210 mL | 0003-1614-12

BARACLUDE Oral Solution is a ready-to-use product; dilution or mixing with water or any other solvent or liquid product is not recommended. Each bottle of the oral solution is accompanied by a dosing spoon that is calibrated in 0.5 mL increments up to 10 mL.

Storage

BARACLUDE Tablets should be stored in a tightly closed container at 25°C (77°F); excursions permitted between 15°C and 30°C (59°F and 86°F) [see USP Controlled Room Temperature]. Store in the outer carton to protect from light.

BARACLUDE Oral Solution should be stored in the outer carton at 25°C (77°F); excursions permitted between 15°C and 30°C (59°F and 86°F) [see USP Controlled Room Temperature]. Protect from light. After opening, the oral solution can be used up to the expiration date on the bottle. The bottle and its contents should be discarded after the expiration date.

17 PATIENT COUNSELING INFORMATION

See FDA-approved patient labeling (Patient Information).

Severe Acute Exacerbation of Hepatitis after Discontinuation of Treatment

Inform patients that discontinuation of anti-hepatitis B therapy, including BARACLUDE, may result in severe acute exacerbations of hepatitis B. Advise the patient to not discontinue BARACLUDE without first informing their healthcare provider [see Warnings and Precautions (5.1)].

Risk of Development of HIV-1 Resistance in Patients with HIV-1 Coinfection

Inform patients that if they have or develop HIV infection and are not receiving effective HIV treatment, BARACLUDE may increase the risk of development of resistance to HIV medication [see Warnings and Precautions (5.2)].

Lactic Acidosis and Severe Hepatomegaly

Lactic acidosis and severe hepatomegaly with steatosis, including fatal cases, have been reported with use of drugs similar to BARACLUDE. Advise patients to contact their healthcare provider immediately and stop BARACLUDE if they develop clinical symptoms suggestive of lactic acidosis or pronounced hepatotoxicity [see Warnings and Precautions (5.3)].

Missed Dosage

Inform patients that it is important to take BARACLUDE on a regular dosing schedule on an empty stomach (at least 2 hours after a meal and 2 hours before the next meal) and to avoid missing doses as it can result in development of resistance [see Dosage and Administration (2.1)].

Treatment Duration

Advise patients that in the treatment of chronic hepatitis B, the optimal duration of treatment is unknown. The relationship between response and long-term prevention of outcomes such as hepatocellular carcinoma is not known.

Instructions for Use

Inform patients using the oral solution to hold the dosing spoon in a vertical position and fill it gradually to the mark corresponding to the prescribed dose. Rinsing of the dosing spoon with water is recommended after each daily dose. Some patients may find it difficult to accurately measure the prescribed dose using the provided dosing spoon; therefore, patients/caregivers should refer to the steps in the Patient Information section that demonstrate the correct technique of using the provided dosing spoon to measure the prescribed BARACLUDE dose.

Pregnancy Registry

Advise patients that there is a pregnancy exposure registry that monitors pregnancy outcomes in women exposed to BARACLUDE during pregnancy [see Use in Specific Populations (8.1)].

Patient Information

BARACLUDE®(BEAR ah klude)

(entecavir)

Tablets

BARACLUDE®(BEAR ah klude)

(entecavir)

Oral Solution

Read this Patient Information before you start taking BARACLUDE and each time you get a refill. There may be new information. This information does not take the place of talking with your healthcare provider about your medical condition or treatment.

What is the most important information I should know about BARACLUDE?

1. Your hepatitis B virus (HBV) infection may get worse if you stop taking BARACLUDE. This usually happens within 6 months after stopping BARACLUDE.

- Take BARACLUDE exactly as prescribed.
- Do not run out of BARACLUDE.
- Do not stop BARACLUDE without talking to your healthcare provider.
- Your healthcare provider should monitor your health and do regular blood tests to check your liver if you stop taking BARACLUDE.

2. If you have or get HIV that is not being treated with medicines while taking BARACLUDE, the HIV virus may develop resistance to certain HIV medicines and become harder to treat. You should get an HIV test before you start taking BARACLUDE and anytime after that when there is a chance you were exposed to HIV.

BARACLUDE can cause serious side effects including:

3. Lactic acidosis (buildup of acid in the blood). Some people who have taken BARACLUDE or medicines like BARACLUDE (a nucleoside analogue) have developed a serious condition called lactic acidosis. Lactic acidosis is a serious medical emergency that can cause death. Lactic acidosis must be treated in the hospital. Reports of lactic acidosis with BARACLUDE generally involved patients who were seriously ill due to their liver disease or other medical condition.

Call your healthcare provider right away if you get any of the following signs or symptoms of lactic acidosis:

- You feel very weak or tired.
- You have unusual (not normal) muscle pain.
- You have trouble breathing.
- You have stomach pain with nausea and vomiting.
- You feel cold, especially in your arms and legs.
- You feel dizzy or light-headed.
- You have a fast or irregular heartbeat.

4. Serious liver problems. Some people who have taken medicines like BARACLUDE have developed serious liver problems called hepatotoxicity, with liver enlargement (hepatomegaly) and fat in the liver (steatosis). Hepatomegaly with steatosis is a serious medical emergency that can cause death.

Call your healthcare provider right away if you get any of the following signs or symptoms of liver problems:

- Your skin or the white part of your eyes turns yellow (jaundice).
- Your urine turns dark.
- Your bowel movements (stools) turn light in color.
- You don’t feel like eating food for several days or longer.
- You feel sick to your stomach (nausea).
- You have lower stomach pain.

You may be more likely to get lactic acidosis or serious liver problems if you are female, very overweight, or have been taking nucleoside analogue medicines, like BARACLUDE, for a long time.

What is BARACLUDE?

BARACLUDE is a prescription medicine used to treat chronic hepatitis B virus (HBV) in adults and children 2 years of age and older who have active liver disease.

- BARACLUDE will not cure HBV.
- BARACLUDE may lower the amount of HBV in the body.
- BARACLUDE may lower the ability of HBV to multiply and infect new liver cells.
- BARACLUDE may improve the condition of your liver.
- It is not known whether BARACLUDE will reduce your chances of getting liver cancer or liver damage (cirrhosis), which may be caused by chronic HBV infection.
- It is not known if BARACLUDE is safe and effective for use in children less than 2 years of age.

What should I tell my healthcare provider before taking BARACLUDE?

Before you take BARACLUDE, tell your healthcare provider if you:

- have kidney problems. Your BARACLUDE dose or schedule may need to be changed.
- have received medicine for HBV before. Some people, especially those who have already been treated with certain other medicines for HBV infection, may develop resistance to BARACLUDE. These people may have less benefit from treatment with BARACLUDE and may have worsening of hepatitis after resistant virus appears. Your healthcare provider will test the level of the hepatitis B virus in your blood regularly.
- have any other medical conditions.
- are pregnant or plan to become pregnant. It is not known if BARACLUDE will harm your unborn baby. Talk to your healthcare provider if you are pregnant or plan to become pregnant.
Antiretroviral Pregnancy Registry. If you take BARACLUDE while you are pregnant, talk to your healthcare provider about how you can take part in the BARACLUDE Antiretroviral Pregnancy Registry. The purpose of the pregnancy registry is to collect information about the health of you and your baby.
- are breastfeeding or plan to breastfeed. It is not known if BARACLUDE can pass into your breast milk. You and your healthcare provider should decide if you will take BARACLUDE or breastfeed.

Tell your healthcare provider about all the medicines you take, including prescription and over-the-counter medicines, vitamins, and herbal supplements. Especially tell your healthcare provider if you have taken a medicine to treat HBV in the past.

Know the medicines you take. Keep a list of your medicines with you to show your healthcare provider and pharmacist when you get a new medicine.

How should I take BARACLUDE?

- Take BARACLUDE exactly as your healthcare provider tells you to.
- Your healthcare provider will tell you how much BARACLUDE to take.
- Your healthcare provider will tell you when and how often to take BARACLUDE.
- Take BARACLUDE on an empty stomach, at least 2 hours after a meal and at least 2 hours before the next meal.
- If you are taking BARACLUDE Oral Solution, or giving it to your child, carefully measure the dose with the dosing spoon provided, as follows:

- Hold the dosing spoon in an upright (vertical) position and slowly fill it to the measurement line on the dosing spoon that is the same as the prescribed dose. Bring the dosing spoon to eye level to be sure that the level of the BARACLUDE Oral Solution is at the correct measurement line (see Figure 1).

Figure 1

- With the dosing spoon at eye level, holding it with the measurement lines facing you, check that it has been filled to the correct measurement line. The top of the BARACLUDE Oral Solution in the dosing spoon will look curved, not flat. Measure the dose of BARACLUDE Oral Solution at the bottom of the curve. Your dose of BARACLUDE Oral Solution is measured correctly when the bottom of the curve is lined up with the measurement line of the prescribed dose. As an example, Figure 2 shows the right way to measure a 5 mL dose of BARACLUDE (see Figure 2).

Figure 2

- BARACLUDE Oral Solution should be swallowed directly from the dosing spoon.
- BARACLUDE Oral Solution should not be mixed with water or any other liquid.
- After each use, rinse the dosing spoon with water and allow it to air dry.
- If you lose the dosing spoon, call your pharmacist or healthcare provider for instructions.
- Do not change your dose or stop taking BARACLUDE without talking to your healthcare provider.
- If you miss a dose of BARACLUDE, take it as soon as you remember and then take your next dose at its regular time. If it is almost time for your next dose, skip the missed dose. Do not take two doses at the same time. Call your healthcare provider or pharmacist if you are not sure what to do.
- When your supply of BARACLUDE starts to run low, call your healthcare provider or pharmacy for a refill. Do not run out of BARACLUDE.
- If you take too much BARACLUDE, call your healthcare provider or go to the nearest emergency room right away.

What are the possible side effects of BARACLUDE?

BARACLUDE may cause serious side effects. See “What is the most important information I should know about BARACLUDE?”

The most common side effects of BARACLUDE include:

- headache
- tiredness
- dizziness
- nausea

Tell your healthcare provider if you have any side effect that bothers you or that does not go away.

These are not all the possible side effects of BARACLUDE. For more information, ask your healthcare provider or pharmacist.

Call your doctor for medical advice about side effects. You may report side effects to the FDA at 1-800-FDA-1088.

How should I store BARACLUDE?

- Store BARACLUDE Tablets or Oral Solution at room temperature, between 68°F and 77°F (20°C and 25°C).
- Keep BARACLUDE Tablets in a tightly closed container.
- Store BARACLUDE Tablets or BARACLUDE Oral Solution in the original carton, and keep the carton out of the light.
- Safely throw away BARACLUDE that is out of date or no longer needed. Dispose of unused medicines through community take-back disposal programs when available or place BARACLUDE in an unrecognizable closed container in the household trash.

Keep BARACLUDE and all medicines out of the reach of children.

General information about the safe and effective use of BARACLUDE

BARACLUDE does not stop you from spreading the hepatitis B virus (HBV) to others by sex, sharing needles, or being exposed to your blood. Talk with your healthcare provider about safe sexual practices that protect your partner. Never share needles. Do not share personal items that can have blood or body fluids on them, like toothbrushes or razor blades. A shot (vaccine) is available to protect people at risk from becoming infected with HBV.

Medicines are sometimes prescribed for purposes other than those listed in a Patient Information leaflet. Do not use BARACLUDE for a condition for which it was not prescribed. Do not give BARACLUDE to other people, even if they have the same symptoms you have. It may harm them.

This Patient Information leaflet summarizes the most important information about BARACLUDE. If you would like more information, talk with your healthcare provider. You can ask your healthcare provider or pharmacist for information about BARACLUDE that is written for health professionals.

For more information, go to www.Baraclude.com or call 1-800-321-1335.

What are the ingredients in BARACLUDE?

Active ingredient: entecavir

Inactive ingredients in BARACLUDE Tablets: lactose monohydrate, microcrystalline cellulose, crospovidone, povidone, magnesium stearate.

Tablet film-coat: titanium dioxide, hypromellose, polyethylene glycol 400, polysorbate 80 (0.5 mg tablet only), and iron oxide red (1 mg tablet only).

Inactive ingredients in BARACLUDE Oral Solution: maltitol, sodium citrate, citric acid, methylparaben, propylparaben, and orange flavor.

Distributed by:

Bristol-Myers Squibb Company

Princeton, NJ 08543 USA

This Patient Information has been approved by the U.S. Food and Drug Administration.

Revised: August 2015

BARACLUDE 0.5 mg Tablets Representative Packaging

See HOW SUPPLIED section for a complete list of available packages of BARACLUDE.

30 Tablets NDC 0003-1611-12
Baraclude®
(entecavir)
Tablets
0.5 mg

Bristol-Myers Squibb

Rx only

BARACLUDE 1 mg Tablets Representative Packaging

30 Tablets NDC 0003-1612-12
Baraclude®
(entecavir)
Tablets
1 mg
Bristol-Myers Squibb
Rx only

BARACLUDE 0.05 mg/mL Oral Solution Representative Packaging

210 mL NDC 0003-1614-12
Baraclude®
(entecavir)
Oral Solution
0.05 mg/mL
Store Bottle in Carton to Protect from Light
Bristol-Myers Squibb
Rx only